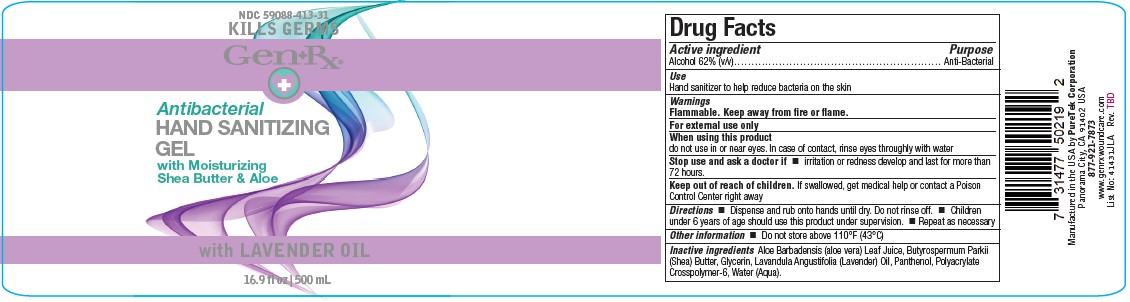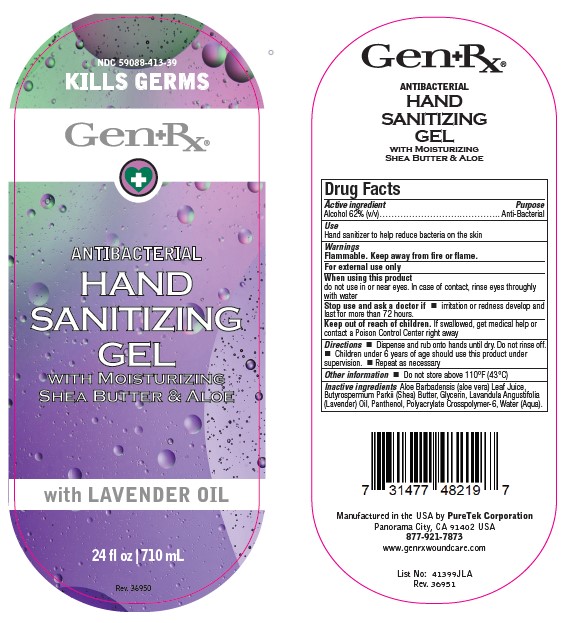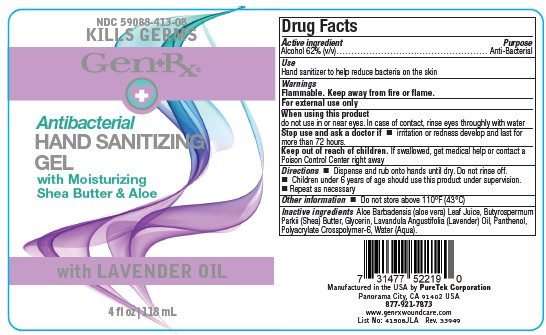 DRUG LABEL: Hand Sanitizing with Lavender Oil
NDC: 59088-413 | Form: GEL
Manufacturer: PureTek Corporation
Category: otc | Type: HUMAN OTC DRUG LABEL
Date: 20241001

ACTIVE INGREDIENTS: ALCOHOL 62 mL/100 mL
INACTIVE INGREDIENTS: ALOE VERA LEAF; GLYCERIN; PANTHENOL; WATER; SHEA BUTTER; METHACRYLIC ACID - ETHYL ACRYLATE COPOLYMER (4500 MPA.S); LAVANDULA ANGUSTIFOLIA FLOWERING TOP

GenRx Hand Sanitizing Gel with Lavender

Active Ingredient

Alcohol 62% (v/v)

Purpose

Anti-Bacterial

Uses

■ Hand sanitizer to help reduce bacteria on the skin

Warnings

■ Flammable. Keep away from fire or flame.

When using this product

■ do not use in or near eyes. In case of contact, rinse eyes throughly with water

Stop use and ask a doctor if

■ irritation or redness develop and last for more than 72 hours

Keep out of reach of children

If swallowed, get medical help or contact a Poison Control Center right away.

Directions

■ Dispense and rub onto hands until dry. Do not rinse off.

■ Children under 6 years of age should use this product under supervision.

■ repeat as necessary

Other information

■ Do not store above 110°F (43°C)

Inactive ingredients

Aloe Barbadensis (aloe vera) Leaf Juice, Butyrospermum Parkii (Shea) Butter, Glycerin, Lavandula Angustifolia (Lavender) Oil, Panthenol, Polyacrylate Crosspolymer-6, Water (Aqua)

GenRx Hand Sanitizing Gel with Lavender

Manufactured in the USA by PureTek Corporation
Panorama City, CA 91402 USA
877-921-7873
www.genrxwoundcare.com

List No:41431JLA

NDC 59088-413-08

NDC 59088-413-31

NDC 59088-413-39